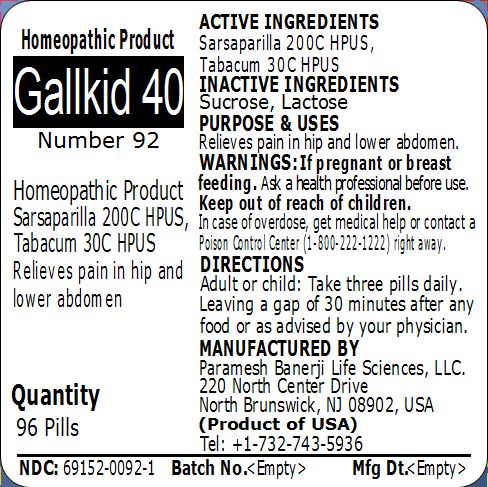 DRUG LABEL: Gallkid 40 (Number 92)
NDC: 69152-0092 | Form: PELLET
Manufacturer: Paramesh Banerji Life Sciences LLC
Category: homeopathic | Type: HUMAN OTC DRUG LABEL
Date: 20150309

ACTIVE INGREDIENTS: SMILAX REGELII ROOT 200 [hp_C]/1 1; TOBACCO LEAF 30 [hp_C]/1 1
INACTIVE INGREDIENTS: SUCROSE; LACTOSE

Active Ingredients

Sarsaparilla 200C HPUS, Tabacum 30C HPUS

Inactive Ingredients

Sucrose, Lactose

Purpose

Relieves pain in hip and lower abdomen

Uses

Relieves pain in hip and lower abdomen

Warnings

If pregnant or breast feeding ask a health professional before use.

Keep out of reach of children. In case of overdose, get medical help or contact a Poison Control Center (1-800-222-1222) right away.

Direction

Adult or child: Take three pills daily. Leaving a gap of 30 minutes after any food or as advised by your physician.

Manufactured by

Paramesh Banerji Life Sciences, LLC

220 North Center Drive

North Brunswick, NJ 08902, USA

Product of USA

Tel: +1-732-743-5936

Principal Display Panel

Homeopathic Product

Gallkid 40

Number 92

Homeopathic Product

Sarsaparilla 200C HPUS, Tabacum 30C HPUS

Relieves pain in hip and lower abdomen

Quantity

96 Pills